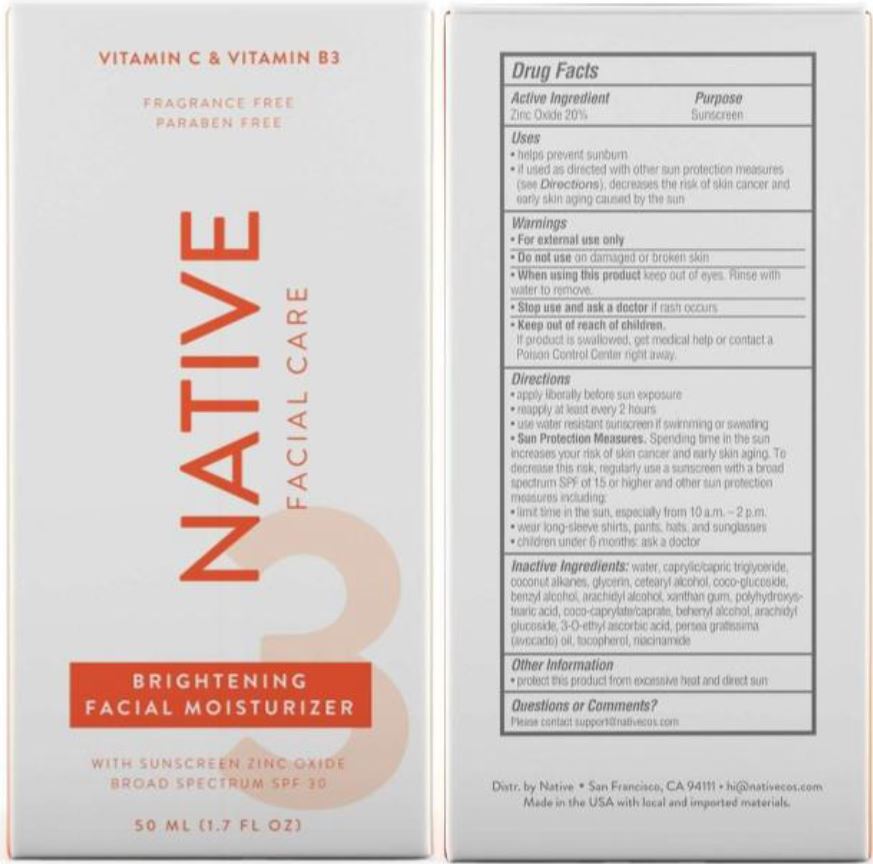 DRUG LABEL: Native Facial Care Brightening Facial Moisturizer Broad Spectrum SPF 30
NDC: 69423-621 | Form: LOTION
Manufacturer: The Procter & Gamble Manufacturing Company
Category: otc | Type: HUMAN OTC DRUG LABEL
Date: 20230928

ACTIVE INGREDIENTS: ZINC OXIDE 20 g/100 mL
INACTIVE INGREDIENTS: AVOCADO OIL; NIACINAMIDE; GLYCERIN; POLYHYDROXYSTEARIC ACID (2300 MW); COCONUT ALKANES; COCO GLUCOSIDE; COCO-CAPRYLATE/CAPRATE; WATER; TOCOPHEROL; DOCOSANOL; CETOSTEARYL ALCOHOL; MEDIUM-CHAIN TRIGLYCERIDES; ARACHIDYL ALCOHOL; ARACHIDYL GLUCOSIDE; BENZYL ALCOHOL; XANTHAN GUM; 3-O-ETHYL ASCORBIC ACID

Native Facial Care Brightening Facial Moisturizer Broad Spectrum SPF 30

Drug Facts

ACTIVE INGREDIENT

ZINC OXIDE 20%

PURPOSE

Sunscreen

Uses

- helps prevent sunburn
- if used as directed with other sun protection measures (see Directions), decreases the risk of skin cancer and early skin aging caused by the sun

Warnings

For external use only

Do not use

- on damaged or broken skin

When using this product

*keep out of eyes. Rinse with water to remove.

Stop use and ask a doctor if

- rash occurs

Keep out of reach of children. If product is swallowed, get medical help or contact a Poison Control Central right away.

Directions

- apply liberally before sun exposure
- reapply at least every 2 hours
- use water resistant sunscreen if swimming or sweating
- Sun Protection Measures. Spending time in the sun increases your risk of skin cancer and early skin aging. To decrease this risk, regularly use a sunscreen with a Broad Spectrum SPF value of 15 or higher and other sun protection measures including:
  - limit time in sun, especially from 10 a.m. – 2 p.m.
  - wear long-sleeved shirts, pants, hats, and sunglasses
- children under 6 months: ask a doctor

Other information

- protect this product from excessive heat and direct sun

Inactive ingredients

Water, Caprylic/Capric Triglyceride, Coconut Alkanes, Glycerin, Cetearyl Alcohol, Coco-Glucoside, Benzyl Alcohol, Arachidyl Alcohol, Xanthan Gum, Polyhydroxystearic Acid, Coco-Caprylate/Caprate, Behenyl Alcohol, Arachidyl Glucoside, 3-0-Ethyl Ascorbic Acid, Persea Gratissima (Avocado) Oil, Tocopherol, Niacinamide

Distr. by Native San Francisco, CA 94111

Questions or comments?

hi @nativecos.com

Made in the USA with local and imported materials

PRINCIPAL DISPLAY PANEL - 50 mL carton

VITAMIN C & VITAMIN B3

FRAGRANCE FREE

PARABEN FREE

NATIVE FACIAL CARE

BRIGHTENING

FACIAL MOISTURIZER

WITH SUNSCREEN ZINC OXIDE

BROAD SPECTRUM SPF 30

50 mL (1.7 FL OZ)